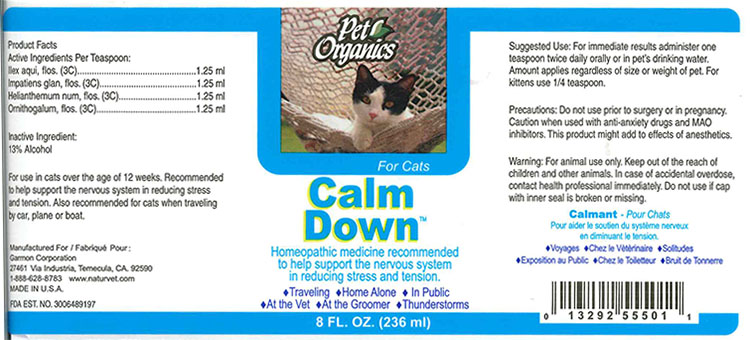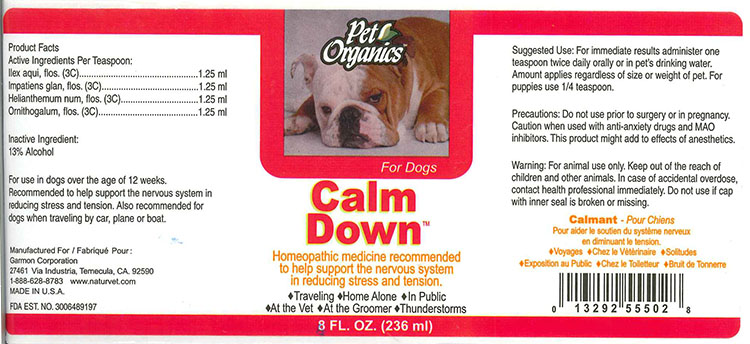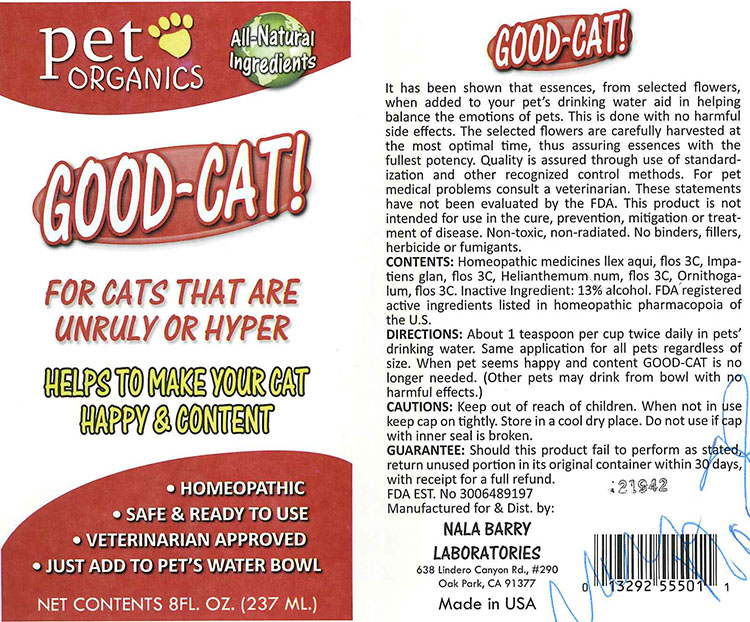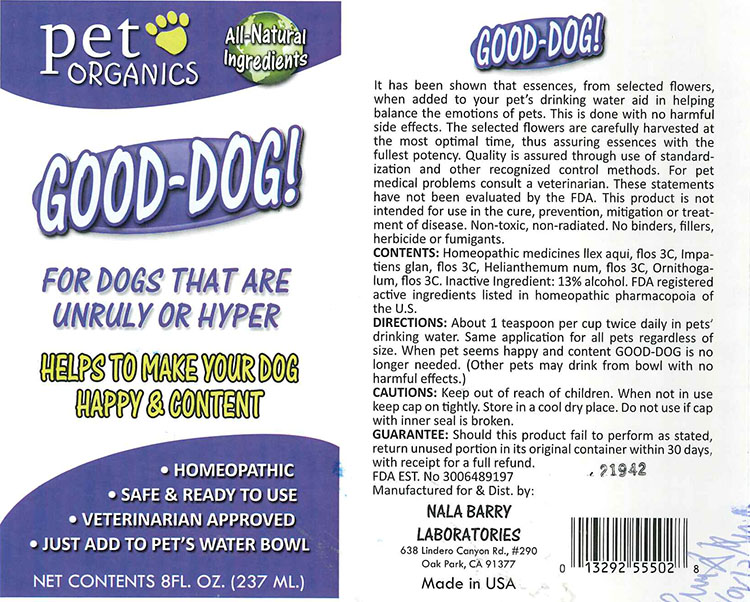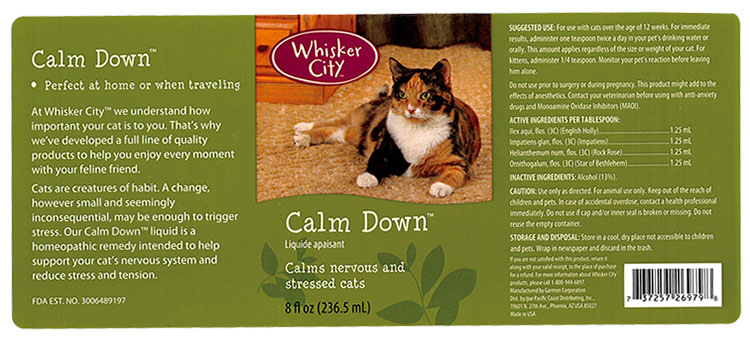 DRUG LABEL: Calm Down Dog/Cat - Good Dog/Cat
NDC: 27135-5550 | Form: LIQUID
Manufacturer: The Garmon Corporation
Category: homeopathic | Type: OTC ANIMAL DRUG LABEL
Date: 20160208

ACTIVE INGREDIENTS: ILEX AQUIFOLIUM FLOWERING TOP 3 [hp_C]/236.5 mL; IMPATIENS GLANDULIFERA FLOWER 3 [hp_C]/236.5 mL; HELIANTHEMUM NUMMULARIUM FLOWER 3 [hp_C]/236.5 mL; ORNITHOGALUM UMBELLATUM FLOWERING TOP 3 [hp_C]/236.5 mL
INACTIVE INGREDIENTS: ALCOHOL

Whisker City Calm Down

ACTIVE INGREDIENTS PER TABLESPOON:

Ilex aqui, flos. (3C) (English Holly)...........................1.25mL
Impatiens glan, flos. (3C) (Impatiens).......................1.25mL
Helianthemum num, flos. (3C) (Rock Rose)..................1.25mL
Ornithogalum, flos. (3C) (Star of Bethlehem).........................1.25mL

INACTIVE INGREDIENTS:

Alcohol (13%)

PURPOSE

Calms nervous and stressed pets. Intended to help support your pet's nervous system and reduce stress and tension.

SUGGESTED USE:

For use with pet over the age of 12 weeks. For immediate results, administer one teaspoon twice a day in your pet's drinking water or orally. This amount applies regardless of size or weight of your pet. For young pets, administer 1/4 teaspoon. Monitor your pet's reaction before leaving him alone.

CAUTION:

Use only as directed. For animal use only. Keep out of reach of children and pets. In case of accidental overdose, contact health professional immediately. Do not use if cap and/or inner seal is broken or missing. Do not reuse the empty container.

PRINCIPAL DISPLAY

CALM DOWN DOG

CALM DOWN CAT

GOOD DOG

GOOD CAT

WHISKER CITY